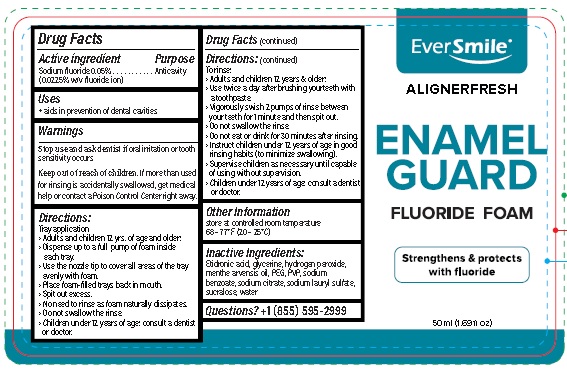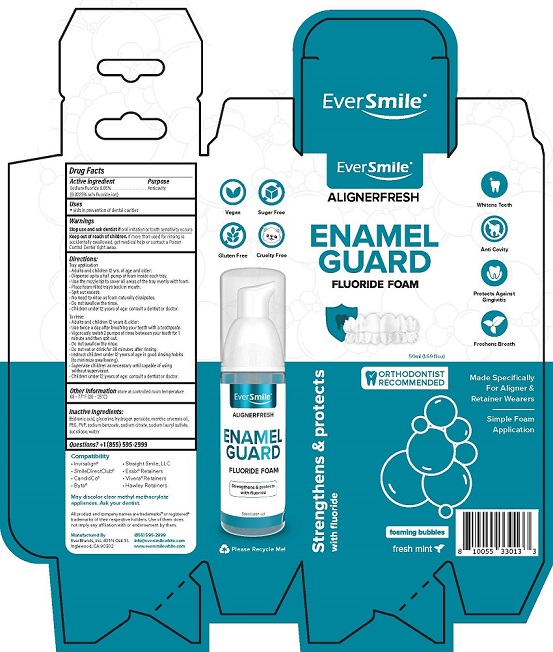 DRUG LABEL: EverSmile AlignerFresh Enamel Guard
NDC: 72655-300 | Form: RINSE
Manufacturer: Everbrands, Inc.
Category: otc | Type: HUMAN OTC DRUG LABEL
Date: 20220329

ACTIVE INGREDIENTS: SODIUM FLUORIDE 0.225 mg/1 mL
INACTIVE INGREDIENTS: ETIDRONIC ACID; GLYCERIN; HYDROGEN PEROXIDE; MENTHA ARVENSIS FLOWER OIL; POLYETHYLENE GLYCOL 8000; POVIDONE K30; SODIUM BENZOATE; SODIUM CITRATE; SODIUM LAURYL SULFATE; SUCRALOSE; WATER

ALIGNERFRESH ENAMEL GUARD FLUORIDE FOAM

DRUG FACTS

Purpose

Anticavity

Active ingredient

Sodium fluoride 0.05%

(0.0225% w/v fluoride ion)

Uses

- aids in prevention of dental cavities

Warnings

Stop use and ask a dentist if oral irritation or tooth sensitivity occurs

Keep out of reach of children. If more than used for rinsing is accidentally

swallowed, get medical help or contact a poison Control Center right away.

Directions:

Tray application

- Adults and children 12 yrs. of age and older:
- Dispense up to a full pump of foam inside each tray.
- Use the nozzle tip to cover all areas of the tray evenly with foam.
- Place form-filled trays back in mouth.
- Spit out excess.
- No need to rinse as foam naturally dissipates.
- Do not swallow rinse.
- Children under 12 years of age: consult a dentist or doctor.

To rinse:

- Adults and children 12 years & older:
- Use twice a day after brushing your teeth with a toothpaste.
- Vigorously swish 2 pumps of rinse between your teeth for 1 minute and then spit out.
- Do not swallow the rinse.
- Do not eat or drink for 30 minutes after rinsing.
- Instruct children under 12 years of age in good rinsing habits (to minimize swallowing).
- Supervise children as necessary until capable of using without supervision.
- Children under 12 years of age: consult a dentist or doctor.

Other Information store at controlled room temperature 68-77°F (20 - 25°C)

Inactive Ingredients:
Etidronic Acid, glycerin, hydrogen peroxide,
menthe arvensis oil, PEG, PVP, sodium
benzoate, sodium citrate, sodium lauryl sulfate.
sucralose, water

Questions? +1 (855) 595-2999

Package Label

EverSmile®

ALIGNERFRESH

ENAMEL
GUARD

FLUORIDE FOAM

50 mL (1.69fl oz)

Manufactured By
EverBrands, Inc. 401 N Oak St.
Inglewood, CA 90302

855 595-2999
info@eversmilewhite.com
www.eversmilewhite.com

res